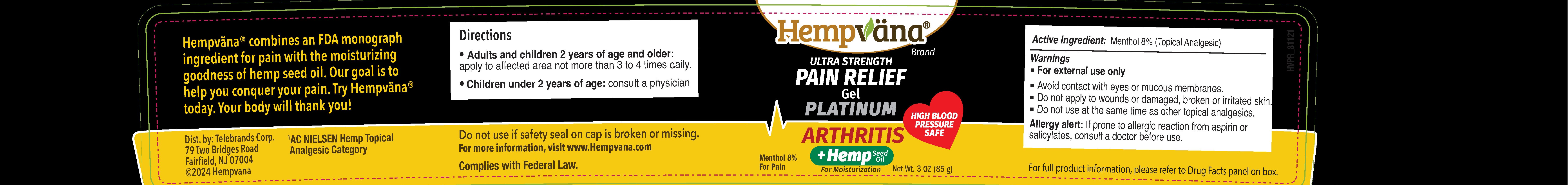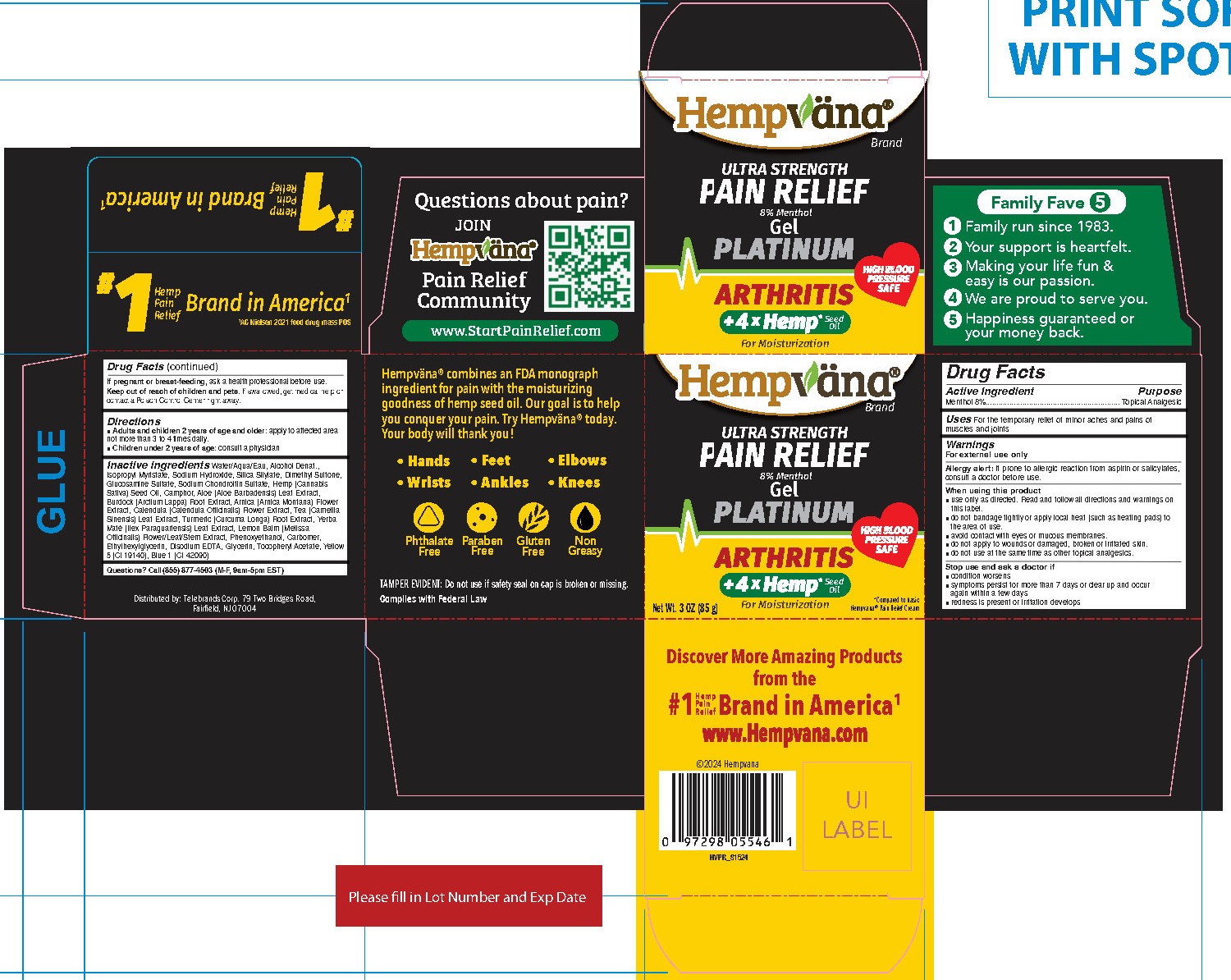 DRUG LABEL: Hempvana Ultra Strength Pain Relief Gel Platinum - Arthritis
NDC: 73287-030 | Form: GEL
Manufacturer: Telebrands Corp
Category: otc | Type: HUMAN OTC DRUG LABEL
Date: 20240902

ACTIVE INGREDIENTS: MENTHOL 8 g/8 g
INACTIVE INGREDIENTS: WATER; ISOPROPYL MYRISTATE; SODIUM HYDROXIDE; SILICON DIOXIDE; ALCOHOL; SODIUM CHONDROITIN SULFATE (PORCINE; 5500 MW); ALOE VERA LEAF; ARCTIUM LAPPA ROOT; ARNICA MONTANA FLOWER; MELISSA OFFICINALIS FLOWERING TOP; PHENOXYETHANOL; EDETATE DISODIUM ANHYDROUS; GLYCERIN; DIMETHYL SULFONE; GLUCOSAMINE SULFATE; CAMPHOR, (-)-; CALENDULA OFFICINALIS FLOWER; GREEN TEA LEAF; TURMERIC; ILEX PARAGUARIENSIS LEAF; CANNABIS SATIVA SEED OIL; CARBOMER HOMOPOLYMER, UNSPECIFIED TYPE; ETHYLHEXYLGLYCERIN; FD&C YELLOW NO. 5; .ALPHA.-TOCOPHEROL ACETATE; FD&C BLUE NO. 1

Hempvana Ultra Strength Pain Relief Gel Platinum - Arthritis

Active Ingredient

Menthol 8%

Purpose

Menthol 8%....................Topical Analgesic

Uses

For the temporary relief of minor aches and pains of muscles and joints

Warnings

For external use only

Allergy alert:If prone to allergic reaction from aspirin or salicylates, consult a doctor before use.

When using this product

- Use only as directed. Read and follow all directions and warnings on this label.
- Do not bandage tightly or apply local heat (such as heating pads) to the area of use.
- Avoid contact with eyes or mucous membranes.
- Do not apply to wounds or damaged, broken or irritated skin.
- Do not use at the same time as other topical analgesics.

Stop use and ask a doctor if

- Condition worsens
- Symptoms persist for more than 7 days or clear up and occur again within a few days
- Redness is present or irritation develops

PREGNANCY OR BREAST FEEDING

If pregnant or breast-feeding,ask a health professional before use.

Keep out of reach of children and pets.If swallowed, get medical help or contact a Poison Control Center right away.

Directions

■ Adults and children 2 years of age and older: apply to affected areanot more than 3 to 4 times daily.

■ Children under 2 years of age: consult a physician

Inactive Ingredients

Water/Aqua/Eau, Alcohol Denat., Isopropyl Myristate, Sodium Hydroxide, Silica Silylate, Dimethyl Sulfone, Glucosamine Sulfate, Sodium Chondroitin Sulfate, Cannabis Sativa (Hemp) Seed Oil, Camphor, Aloe Barbadensis Leaf Extract, Arctium Lappa Root Extract, Arnica Montana Flower Extract, Calendula Officinalis Flower Extract, Camellia Sinensis Leaf Extract, Curcuma Longa (Turmeric) Root Extract, Ilex Paraguariensis Leaf Extract, Melissa Officinalis Flower/Leaf/Stem Extract, Phenoxyethanol, Carbomer, Ethylhexylglycerin, Disodium EDTA, Glycerin, Tocopheryl Acetate, Yellow 5 (CI 19140), Blue 1 (CI 42090)

Questions?

Questions? Call (855) 877-4503 (M-F, 9am-5pm EST)

PACKAGE LABEL

Hempvana

Ultra Strength

Pain Relief

Menthol 8%

Gel

Platinum

Arthritis

+ 4 x Hemp Seed Oil for Moisturization

Net Wt. 3 OZ (85 g)